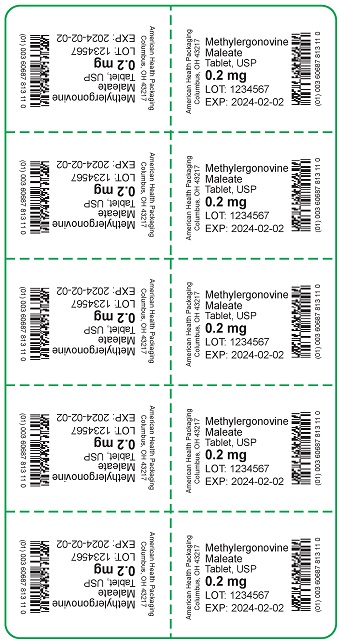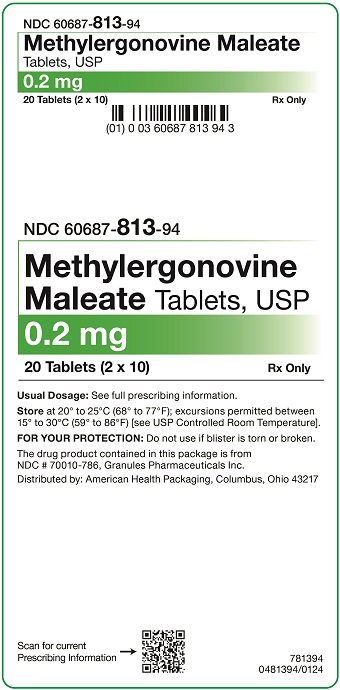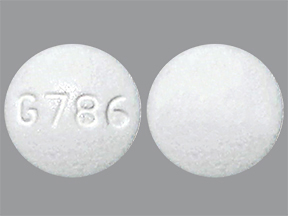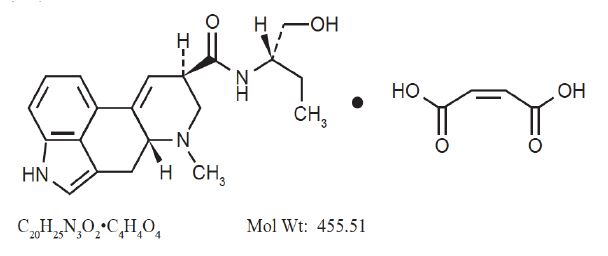 DRUG LABEL: Methylergonovine Maleate
NDC: 60687-813 | Form: TABLET
Manufacturer: American Health Packaging
Category: prescription | Type: HUMAN PRESCRIPTION DRUG LABEL
Date: 20251113

ACTIVE INGREDIENTS: METHYLERGONOVINE MALEATE 0.2 mg/1 1
INACTIVE INGREDIENTS: ACACIA; STARCH, CORN; GELATIN, UNSPECIFIED; LACTOSE MONOHYDRATE; METHYLPARABEN; MICROCRYSTALLINE CELLULOSE; POVIDONE, UNSPECIFIED; PROPYLPARABEN; STEARIC ACID; TARTARIC ACID

Methylergonovine Maleate Tablets, USP
Rx Only
8481394/0124F

DESCRIPTION

Methylergonovine Maleate Tablets, USP is a semi-synthetic ergot alkaloid used for the prevention and control of postpartum hemorrhage.

Methylergonovine Maleate Tablets, USP is available in tablets for oral ingestion containing 0.2 mg methylergonovine maleate.

Tablets
Active ingredient: Methylergonovine maleate, USP, 0.2 mg.

Inactive ingredients: acacia, corn starch, gelatin, lactose monohydrate, methylparaben, microcrystalline cellulose, povidone, propylparaben, stearic acid, and tartaric acid.

Chemically, methylergonovine maleate is designated as ergoline-8-carboxamide, 9,10-didehydro-N-[1-(hydroxymethyl) propyl]-6-methyl-,[8β(S)]-,(Z)-2-butenedioate(1:1) (salt). Its structural formula is:

CLINICAL PHARMACOLOGY

Methylergonovine maleate acts directly on the smooth muscle of the uterus and increases the tone, rate, and amplitude of rhythmic contractions. Thus, it induces a rapid and sustained tetanic uterotonic effect which shortens the third stage of labor and reduces blood loss. The onset of action after I.V. administration is immediate; after I.M. administration, 2 to 5 minutes, and after oral administration, 5 to 10 minutes.

Pharmacokinetic studies following an I.V. injection have shown that methylergonovine is rapidly distributed from plasma to peripheral tissues within 2 to 3 minutes or less. The bioavailability after oral administration was reported to be about 60% with no accumulation after repeated doses. During delivery, with intramuscular injection, bioavailability increased to 78 %. Ergot alkaloids are mostly eliminated by hepatic metabolism and excretion, and the decrease in bioavailability following oral administration is probably a result of first-pass metabolism in the liver.

Bioavailability studies conducted in fasting healthy female volunteers have shown that oral absorption of a 0.2 mg methylergonovine tablet was fairly rapid with a mean peak plasma concentration of 3243 ± 1308 pg/mL observed at 1.12 ± 0.82 hours. For a 0.2 mg intramuscular injection, a mean peak plasma concentration of 5918 ± 1952 pg/mL was observed at 0.41 ± 0.21 hours. The extent of absorption of the tablet, based upon methylergonovine plasma concentrations, was found to be equivalent to that of the I.M. solution given orally, and the extent of oral absorption of the I.M. solution was proportional to the dose following administration of 0.1, 0.2, and 0.4 mg. When given intramuscularly, the extent of absorption of methylergonovine maleate solution was about 25 % greater than the tablet. The volume of distribution (Vdss/F) of methylergonovine was calculated to be 56.1 ± 17.0 liters, and the plasma clearance (CLp/F) was calculated to be 14.4 ± 4.5 liters per hour. The plasma level decline was biphasic with a mean elimination half-life of 3.39 hours (range 1.5 to 12.7 hours). A delayed gastrointestinal absorption (Tmax about 3 hours) of methylergonovine maleate tablet might be observed in postpartum women during continuous treatment with this oxytocic agent.

INDICATIONS & USAGE

Following delivery of placenta, for routine management of uterine atony, hemorrhage and subinvolution of the uterus. For control of uterine hemorrhage in the second stage of labor following delivery of the anterior shoulder.

CONTRAINDICATIONS

Hypertension; toxemia; pregnancy; and hypersensitivity.

WARNINGS

General
This drug should not be administered I.V. routinely because of the possibility of inducing sudden hypertensive and cerebrovascular accidents. If I.V administration is considered essential as a lifesaving measure, methylergonovine maleate should be given slowly over a period of no less than 60 seconds with careful monitoring of blood pressure. Intra-arterial or periarterial injection should be strictly avoided.

Caution should be exercised in presence of impaired hepatic or renal function.

Breast-feeding
Mothers should not breast-feed during treatment with methylergonovine maleate. Milk secreted during this period should be discarded. Methylergonovine maleate may produce adverse effects in the breast-feeding infant. Methylergonovine maleate may also reduce the yield of breast milk. Mothers should wait at least 12 hours after administration of the last dose of methylergonovine maleate before initiating or resuming breast feeding.

Coronary artery disease
Patients with coronary artery disease or risk factors for coronary artery disease (e.g., smoking, obesity, diabetes, high cholesterol) may be more susceptible to developing myocardial ischemia and infarction associated with methylergonovine-induced vasospasm.

Medication errors
Inadvertent administration of methylergonovine maleate to newborn infants has been reported. In these cases of inadvertent neonatal exposure, symptoms such as respiratory depression, convulsions, cyanosis and oliguria have been reported. Usual treatment is symptomatic. However, in severe cases, respiratory and cardiovascular support is required.

Methylergonovine maleate has been administered instead of vitamin K and Hepatitis B vaccine, medications which are routinely administered to the newborn. Due to the potential for accidental neonatal exposure, methylergonovine maleate injection should be stored separately from medications intended for neonatal administration.

PRECAUTIONS

General

Caution should be exercised in the presence of sepsis, obliterative vascular disease. Also use with caution during the second stage of labor. The necessity for manual removal of a retained placenta should occur only rarely with proper technique and adequate allowance of time for its spontaneous separation.

Drug Interactions

CYP 3A4 inhibitors (e.g., Macrolide Antibiotics and Protease Inhibitors)
There have been rare reports of serious adverse events in connection with the coadministration of certain ergot alkaloid drugs (e.g., dihydroergotamine and ergotamine) and potent CYP 3A4 inhibitors, resulting in vasospasm leading to cerebral ischemia and/or ischemia of the extremities. Although there have been no reports of such interactions with methylergonovine alone, potent CYP 3A4 inhibitors should not be coadministered with methylergonovine. Examples of some of the more potent CYP 3A4 inhibitors include macrolide antibiotics (e.g., erythromycin, troleandomycin, clarithromycin), HIV protease or reverse transcriptase inhibitors (e.g., ritonavir, indinavir, nelfinavir, delavirdine) or azole antifungals (e.g., ketoconazole, itraconazole, voriconazole). Less potent CYP 3A4 inhibitors should be administered with caution. Less potent inhibitors include saquinavir, nefazodone, fluconazole, grapefruit juice, fluoxetine, fluvoxamine, zileuton, and clotrimazole. These lists are not exhaustive, and the prescriber should consider the effects on CYP 3A4 of other agents being considered for concomitant use with methylergonovine.

CYP3A4 inducers
Drugs (e.g. nevirapine, rifampicin) that are strong inducers of CYP3A4 are likely to decrease the pharmacological action of methylergonovine maleate.

Beta-blockers
Caution should be exercised when methylergonovine maleate is used concurrently with beta-blockers. Concomitant administration with beta-blockers may enhance the vasoconstrictive action of ergot alkaloids.

Anesthetics
Anesthetics like halothan and methoxyfluran may reduce the oxytocic potency of methylergonovine maleate.

Glyceryl trinitrate and other antianginal drugs
Methylergonovine maleate produces vasoconstriction and can be expected to reduce the effect of glyceryl trinitrate and other antianginal drugs.

No pharmacokinetic interactions involving other cytochrome P450 isoenzymes are known.

Caution should be exercised when methylergonovine maleate is used concurrently with other vasoconstrictors, ergot alkaloids, or prostaglandins.

Carcinogenesis, Mutagenesis, Impairment of Fertility

No long-term studies have been performed in animals to evaluate carcinogenic potential. The effect of the drug on mutagenesis or fertility has not been determined.

Pregnancy

Category C:Animal reproductive studies have not been conducted with methylergonovine maleate. It is also not known whether methylergonovine maleate can cause fetal harm or can affect reproductive capacity. Use of methylergonovine maleate is contraindicated during pregnancy because of its uterotonic effects. (See INDICATIONS AND USAGE).

Labor and Delivery

The uterotonic effect of methylergonovine maleate is utilized after delivery to assist involution and decrease hemorrhage, shortening the third stage of labor.

Nursing Mothers

Mothers should not breast-feed during treatment with methylergonovine maleate and at least 12 hours after administration of the last dose. Milk secreted during this period should be discarded.

Pediatric Use

Safety and effectiveness in pediatric patients have not been established.

Geriatric Use

Clinical studies of methylergonovine maleate did not include sufficient number of subjects aged 65 and over to determine whether they respond differently from younger subjects. Other reported clinical experience has not identified differences in response between the elderly and younger patients. In general dose selection for an elderly patient should be cautious, usually starting at the low end of the dosing range, reflecting the greater frequency of decreased hepatic, renal, or cardiac function, and of concomitant disease or other drug therapy.

ADVERSE REACTIONS

The most common adverse reaction is hypertension associated in several cases with seizure and/or headache. Hypotension has also been reported. Abdominal pain (caused by uterine contractions), nausea and vomiting have occurred occasionally. Rarely observed reactions have included: acute myocardial infarction, transient chest pains, vasoconstriction, vasospasm, coronary arterial spasm, bradycardia, tachycardia, dyspnea, hematuria, thrombophlebitis, water intoxication, hallucinations, leg cramps, dizziness, tinnitus, nasal congestion, diarrhea, diaphoresis, palpitation, rash, and foul taste.

There have been rare isolated reports of anaphylaxis, without a proven causal relationship to the drug product.

Postmarketing Experience
The following adverse drug reactions have been derived from post-marketing experience with methylergonovine maleate via spontaneous case reports. Because these reactions are reported voluntarily from a population of uncertain size, it is not possible to reliably estimate their frequency which is therefore categorized as not known.

Nervous system disorders
Cerebrovascular accident, paraesthesia

Cardiac disorders
Ventricular fibrillation, ventricular tachycardia, angina pectoris, atrioventricular block

DRUG ABUSE AND DEPENDENCE

Methylergonovine maleate has not been associated with drug abuse or dependence of either a physical or psychological nature.

OVERDOSAGE

Symptoms of acute overdose may include: nausea, vomiting, oliquria, abdominal pain, numbness, tingling of the extremities, rise in blood pressure, in severe cases followed by hypotension, respiratory depression, hypothermia, convulsions, and coma.

Because reports of overdosage with methylergonovine maleate are infrequent, the lethal dose in humans has not been established. The oral LD50 (in mg/kg) for the mouse is 187, the rat 93, and the rabbit 4.5. Several cases of accidental methylergonovine maleate injection in newborn infants have been reported, and in such cases 0.2 mg represents an overdose of great magnitude. However, recovery occurred in all but one case following a period of respiratory depression, hypothermia, hypertonicity with jerking movements, and convulsions.

Also, several children 1 to 3 years of age have accidentally ingested up to 10 tablets (2 mg) with no apparent ill effects. A postpartum patient took 4 tablets at one time in error and reported paresthesias and clamminess as her only symptoms.

Treatment of acute overdosage is symptomatic and includes the usual procedures of:

1. removal of offending drug by inducing emesis, gastric lavage, catharsis, and supportive diuresis.
2. maintenance of adequate pulmonary ventilation, especially if convulsions or coma develop.
3. correction of hypotension with pressor drugs as needed.
4. control of convulsions with standard anticonvulsant agents.
5. control of peripheral vasospasm with warmth to the extremities if needed.

DOSAGE & ADMINISTRATION

Orally
One tablet, 0.2 mg, 3 or 4 times daily in the puerperium for a maximum of 1 week.

HOW SUPPLIED

White, round, biconvex compressed tablets debossed with “G 786” on one side and plain on the other side. Available in:
Unit dose packages of 20 (2 x 10) NDC 60687-813-94

Store and Dispense
Tablets: Store at 20° to 25°C (68° to 77°F). [see USP Controlled Room Temperature].

FOR YOUR PROTECTION: Do not use if blister is torn or broken.

PACKAGING INFORMATION

American Health Packaging unit dose blisters (see How Supplied section) contain drug product from Granules Pharmaceuticals Inc. as follows:
(0.2 mg / 20 UD) NDC 60687-813-94 packaged from NDC 70010-786

Distributed by:
American Health Packaging
Columbus, OH 43217

8481394/0124F

Package/Label Display Panel – Carton – 0.2 mg

NDC 60687- 813-94

Methylergonovine
Maleate Tablets, USP

0.2 mg

20 Tablets (2 x 10) Rx Only

Usual Dosage: See full prescribing information.

Store at 20° to 25°C (68° to 77°F); excursions permitted between
15° to 30°C (59° to 86°F) [see USP Controlled Room Temperature].

FOR YOUR PROTECTION: Do not use if blister is torn or broken.

The drug product contained in this package is from
NDC # 70010-786, Granules Pharmaceuticals Inc.

Distributed by: American Health Packaging, Columbus, Ohio 43217

781394
0481394/0124

Package/Label Display Panel – Blister – 0.2 mg

Methylergonovine
Maleate
Tablet, USP

0.2 mg